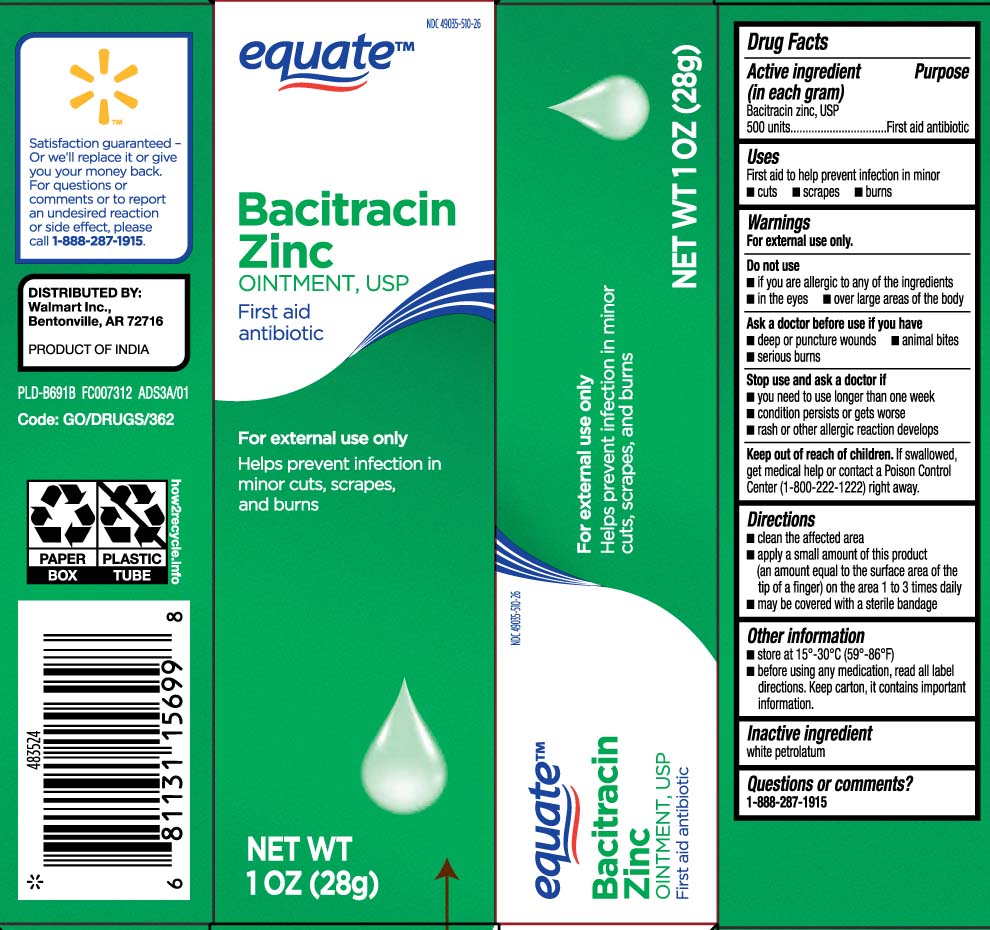 DRUG LABEL: Bacitracin Zinc
NDC: 49035-510 | Form: OINTMENT
Manufacturer: EQUATE (Wal-Mart Stores, Inc.) (see also WAL-MART INC)
Category: otc | Type: HUMAN OTC DRUG LABEL
Date: 20240319

ACTIVE INGREDIENTS: BACITRACIN ZINC 500 [USP'U]/1 g
INACTIVE INGREDIENTS: PETROLATUM

Bacitracin Zinc Oint USP Walmart part333B

Active ingredient (in each gram)

Bacitracin zinc, USP 500 units

Purpose

First aid antibiotic

Uses

First aid to help prevent infection in minor

- cuts
- scrapes
- burns

Warnings

For external use only

Do not use

- if you are allergic to any of the ingredients
- in the eyes
- over large areas of the body

Ask a doctor before use if you have

- deep or puncture wounds
- animal bites
- serious burns

Stop use and ask a doctor if

- you need to use longer than one week
- condition persists or get worse
- rash or other allergic reaction develops

Keep out of reach of children.

If swallowed, get medical help or contact a Poison Control Center (1-800-222-1222) right away.

Directions

- clean the affected area
- apply a small amount of this product (an amount equal to the surface area of the tip of a finger) on the area 1 to 3 times daily
- may be covered with a sterile bandage

Other information

- store at 15º - 30ºC (59º- 86ºF)
- before using any medication, read all label directions. Keep carton, it contains important information.

Inactive ingredients

white petrolatum

Questions or comments?

1-888-287-1915

Principal display panel

Bacitracin Zinc

OINTMENT, USP

First aid antibiotic

For external use only

Help prevent infection in minor cuts, scrapes, and burns

NET WT OZ (g)

DISTRIBUTED BY:

Walmart Inc.,

Bentonville, AR 72716

Package label

EQUATE Bacitracin Zinc Ointment